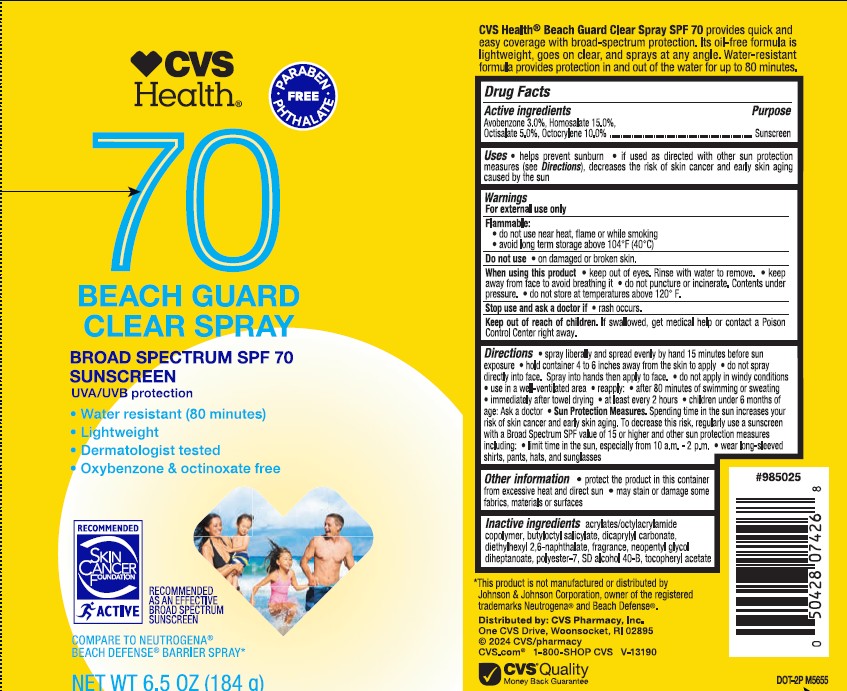 DRUG LABEL: CVS Health SPF 70 Beach Guard Clear
NDC: 51316-076 | Form: SPRAY
Manufacturer: CVS Pharmacy
Category: otc | Type: HUMAN OTC DRUG LABEL
Date: 20250324

ACTIVE INGREDIENTS: AVOBENZONE 30 mg/1 g; HOMOSALATE 150 mg/1 g; OCTISALATE 50 mg/1 g; OCTOCRYLENE 100 mg/1 g
INACTIVE INGREDIENTS: ALCOHOL; ACRYLATE/ISOBUTYL METHACRYLATE/N-TERT-OCTYLACRYLAMIDE COPOLYMER (75000 MW); .ALPHA.-TOCOPHEROL ACETATE; BUTYLOCTYL SALICYLATE; NEOPENTYL GLYCOL DIHEPTANOATE; DICAPRYLYL CARBONATE; POLYESTER-7; DIETHYLHEXYL 2,6-NAPHTHALATE

CVS Health SPF 70 Beach Guard Clear Spray

Active ingredients

Avobenzone 3.0%, Homosalate 15.0%, Octisalate 5.0%, Octocrylene 10.0%,

Purpose

Sunscreen

Uses

- helps prevent sunburn
- if used as directed with other sun protection measures (see Directions), decreases the risk of skin cancer and early skin aging caused by the sun

Warnings

For external use only

Flammable:

• do not use near heat, flame or while smoking
• avoid long term storage above 104°F (40°C)

Do not use

- on damaged or broken skin

When using this product

• keep out of eyes. Rinse with water to remove. • keepaway from face to avoid breathing • do not puncture or incinerate. Contents under pressure. • do not store at temperatures above 120° F.

Stop use and ask doctor if

- rash occurs.

Keep out of reach of children.

If swallowed, get medical help or contact a Poison Control Center right away.

Directions

• apply liberally and spread evenly by hand 15 minutes before sun exposure
• hold can 4 to 6 inches away from the skin to apply
• do not spray directly into face
• do not apply in windy areas

• use in a well ventilated area
• reapply:

- after 80 minutes of swimming or sweating
- immediately after towel drying
- at least every 2 hours
- children under 6 months of age: Ask a doctor
- Sun Protection Measures. Spending time in the sun increases your risk of skin cancer and early skin aging. To decrease this risk, regularly use a sunscreen with a Broad Spectrum SPF value of 15 or higher and other sun protection measures including:

• limit time in the sun, especially from 10 a.m. - 2 p.m.
• wear long-sleeved shirts, pants, hats, and sunglasses

Other Information

• protec the product in this container from excessive heat and direct sun
• may stain or damage some fabrics, materials or surfaces

Inactive ingredients

acrylates/octylacrylamide copolymer, butyloctyl salicylate, dicaprylyl carbonate, diethylhexyl 2,6-naphthalate, fragrance, neopentyl glycol diheptanoate, polyester-7, SD alcohol 40-B, tocopheryl acetate